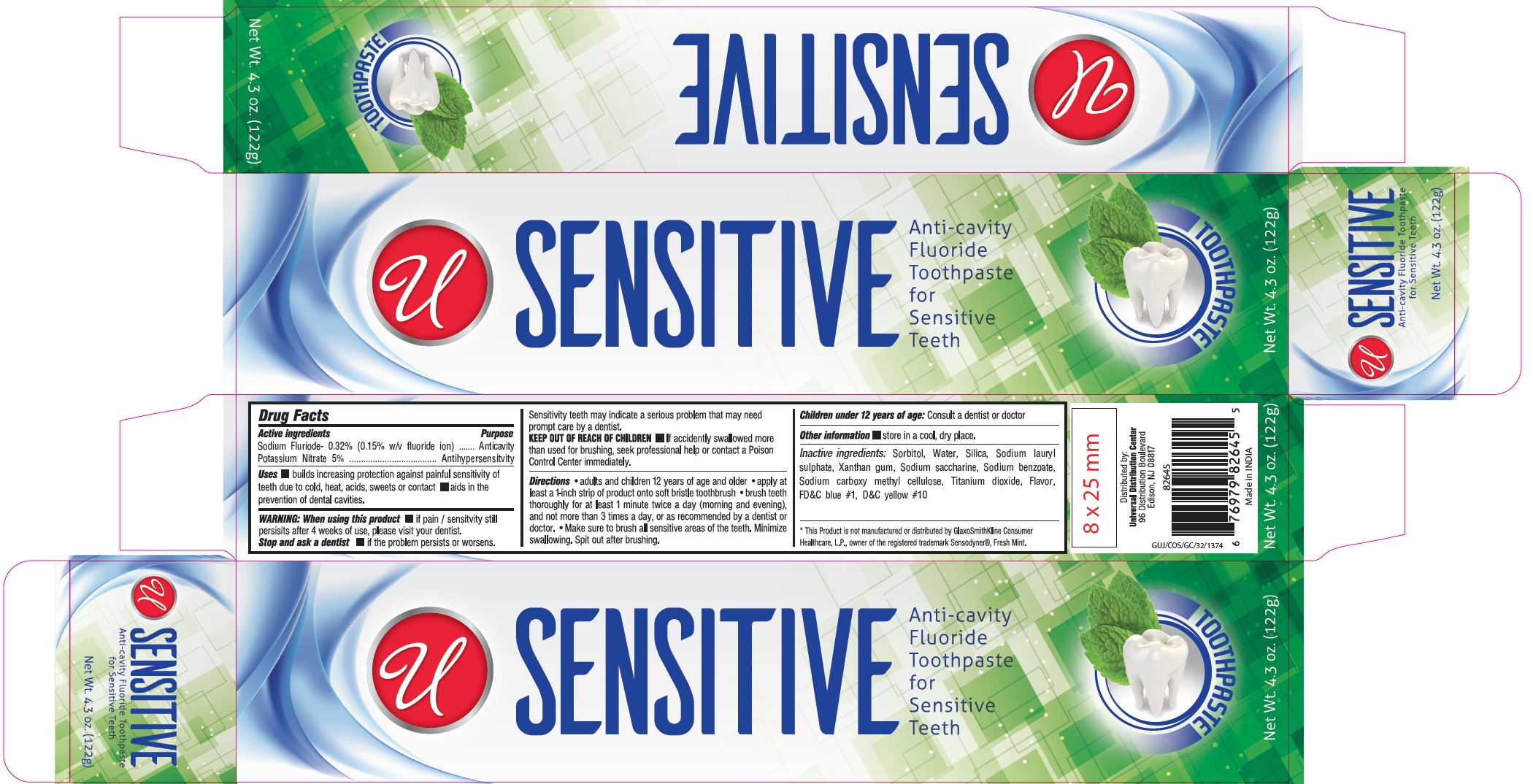 DRUG LABEL: UNIVERSAL SENSITIVE ANTI-CAVITY FLUORIDE
NDC: 52000-109 | Form: PASTE
Manufacturer: Universal Distribution Center LLC
Category: otc | Type: HUMAN OTC DRUG LABEL
Date: 20231117

ACTIVE INGREDIENTS: POTASSIUM NITRATE 5 g/100 g; SODIUM FLUORIDE 0.15 g/100 g
INACTIVE INGREDIENTS: SORBITOL; WATER; SILICON DIOXIDE; SODIUM LAURYL SULFATE; XANTHAN GUM; SACCHARIN SODIUM; SODIUM BENZOATE; CARBOXYMETHYLCELLULOSE SODIUM, UNSPECIFIED; TITANIUM DIOXIDE; FD&C BLUE NO. 1; D&C YELLOW NO. 10

UNIVERSAL SENSITIVE ANTI-CAVITY FLUORIDE TOOTHPASTE

Active Ingredients

Potassium Nitrate 5%

Sodium Fluoride- 0.32% (0.15% w/v fluoride ion)

Purpose

Antihypersensitivity

Anticavity

Uses

- builds increasing protection against painful sensitivity of teeth due to cold, heat, acids, sweets or contact.
- aids in the prevention of dental cavities.

Warning

When using this product

- if pain\ sensitivity still persists after 4 weeks of use, please visit your dentist.

Stop and ask a dentist

- if the problem persists or worsens.

Sensitivity teeth may indicate a serious problem that may need prompt care by a dentist.

Keep out of reach of children

- If accidentally swallowed more than used for brushing, seek professional help or contact a Poison Control Center immediately.

Directions

- adults and children 12 years of age and older
- apply at least a 1-inch strip of product onto soft bristle toothbrush
- brush teeth thoroughly for at least 1 minute twice a day (morning and evening), and not more than 3 times day, or as recommended by a dentist or doctor.
- make sure to brush all sensitive areas of the teeth. Minimize swallowing. Spit out after brushing.

Children under 12 years of age: Consult a dentist or doctor.

Other information

- store in a cool, dry place.

Inactive Ingredients

Sorbitol, Water, Silica, Sodium lauryl sulfate, Xanthan gum, Sodium saccharin, Sodium benzoate, Sodium carboxy methyl cellulose, Titanium dioxide, Flavor, D&C yellow#10, FD&C blue#1

PACKAGE LABEL

PRINCIPAL DISPLAY PANEL

UNIVERSAL SENSITIVE ANTI-CAVITY FLUORIDE TOOTHPASTE